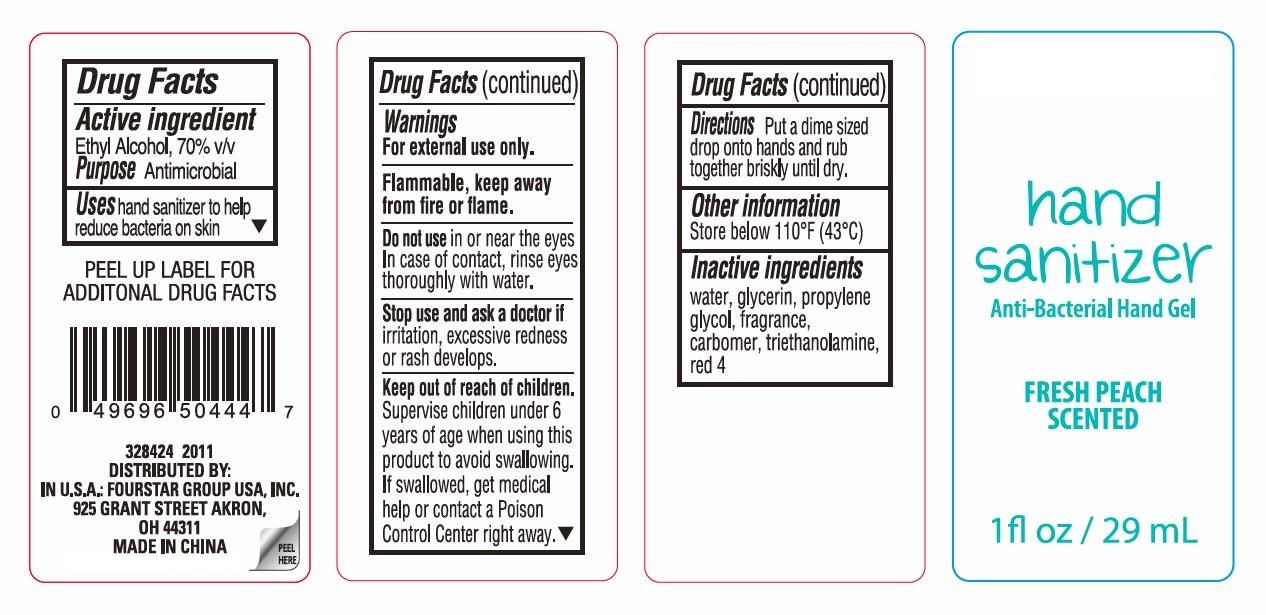 DRUG LABEL: Fresh Peach Scented Antibacterial Hand Sanitizer
NDC: 80684-004 | Form: GEL
Manufacturer: Fourstar Group USA, Inc.
Category: otc | Type: HUMAN OTC DRUG LABEL
Date: 20231026

ACTIVE INGREDIENTS: ALCOHOL 0.7 mL/1 mL
INACTIVE INGREDIENTS: WATER; GLYCERIN; PROPYLENE GLYCOL; CARBOMER HOMOPOLYMER, UNSPECIFIED TYPE; TROLAMINE; FD&C RED NO. 4

Fresh Peach Scented Antibacterial Hand Sanitizer Gel

Active ingredient

Ethyl Alcohol, 70% v/v

Purpose

Antimicrobial

Uses

hand sanitizer to help reduce bacteria on skin

Warnings

For external use only.

Flammable, keep away from fire or flame.

Do not use

in or near the eyes In case of contact, rinse eyes thoroughly with water.

Stop use and ask a doctor if

irritation, excessive redness or rash develops.

Keep out of reach of children.

Supervise children under 6 years of age when using this product to avoid swallowing. If swallowed, get medical help or contact a Poison Control Center right away.

Directions

Put a dime sized drop onto hands and rub together briskly until dry.

Other information

Store below 110°F (43°C)

Inactive ingredients

water, glycerin, propylene glycol, fragrance, carbomer, triethanolamine, red 4